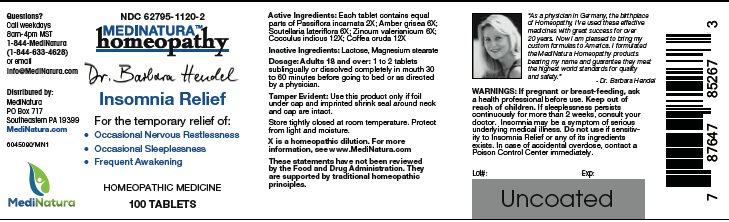 DRUG LABEL: Hendel Insomnia Relief
NDC: 62795-1120 | Form: TABLET
Manufacturer: MediNatura Inc
Category: homeopathic | Type: HUMAN OTC DRUG LABEL
Date: 20230216

ACTIVE INGREDIENTS: PASSIFLORA INCARNATA FLOWERING TOP 2 [hp_X]/1 1; AMBERGRIS 6 [hp_X]/1 1; SCUTELLARIA LATERIFLORA 6 [hp_X]/1 1; ZINC VALERATE DIHYDRATE 6 [hp_X]/1 1; ANAMIRTA COCCULUS SEED 12 [hp_X]/1 1; ARABICA COFFEE BEAN 12 [hp_X]/1 1
INACTIVE INGREDIENTS: LACTOSE MONOHYDRATE; MAGNESIUM STEARATE

Hendel Insomnia Relief

WARNINGS

If pregnant or breast-feeding, ask a health professional before use. Keep out of reach of children. If sleeplessness persists continuously for more than 2 weeks, consult your doctor. Insomnia may be a symptom of serious underlying medical illness. Do not use if sensitivity to Insomnia Relief or any of its ingredients exists. In case of accidental overdose, contact a Poison Control Center immediately.

ACTIVE INGREDIENT

Each tablet contains equal parts of Passiflora incarnata 2X; Amber grisea 6X; Scutellaria lateriflora 6X; Zincum valerianicum 6X; Cocculus indicus 12X; Coffea cruda 12X

INACTIVE INGREDIENT

Lactose, Magnesium stearate

Directions

Adults 18 and over: 1 to 2 tablets sublingually or dissolved completely in mouth 30 to 60 minutes before going to bed or as directed
by a physician.

KEEP OUT OF REACH OF CHILDREN

Uses

For the temporary relief of:
• Occasional Nervous Restlessness
• Occasional Sleeplessness
• Frequent Awakening

PURPOSE

Insomnia Relief

PACKAGE LABEL

Add image transcription here...